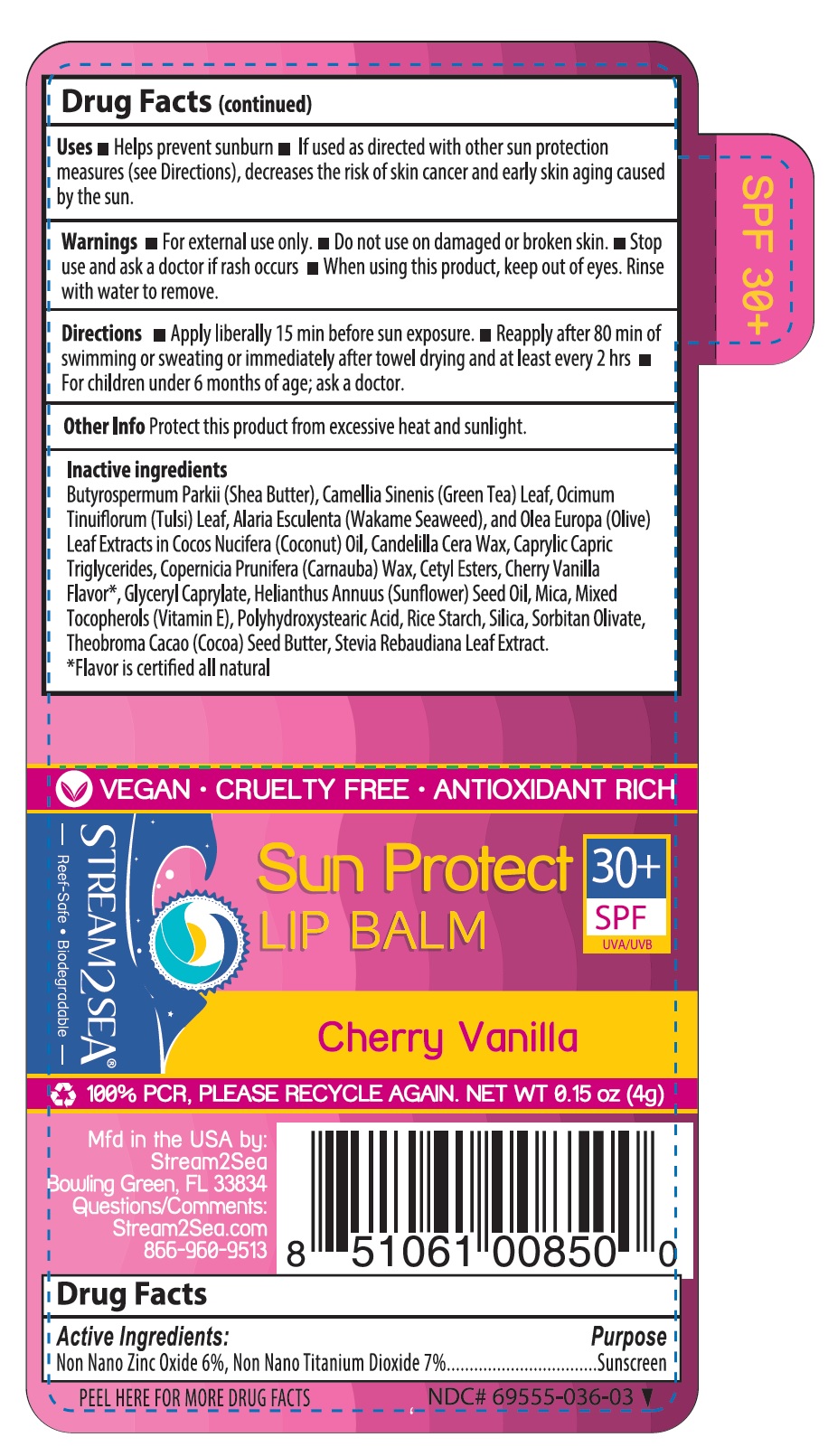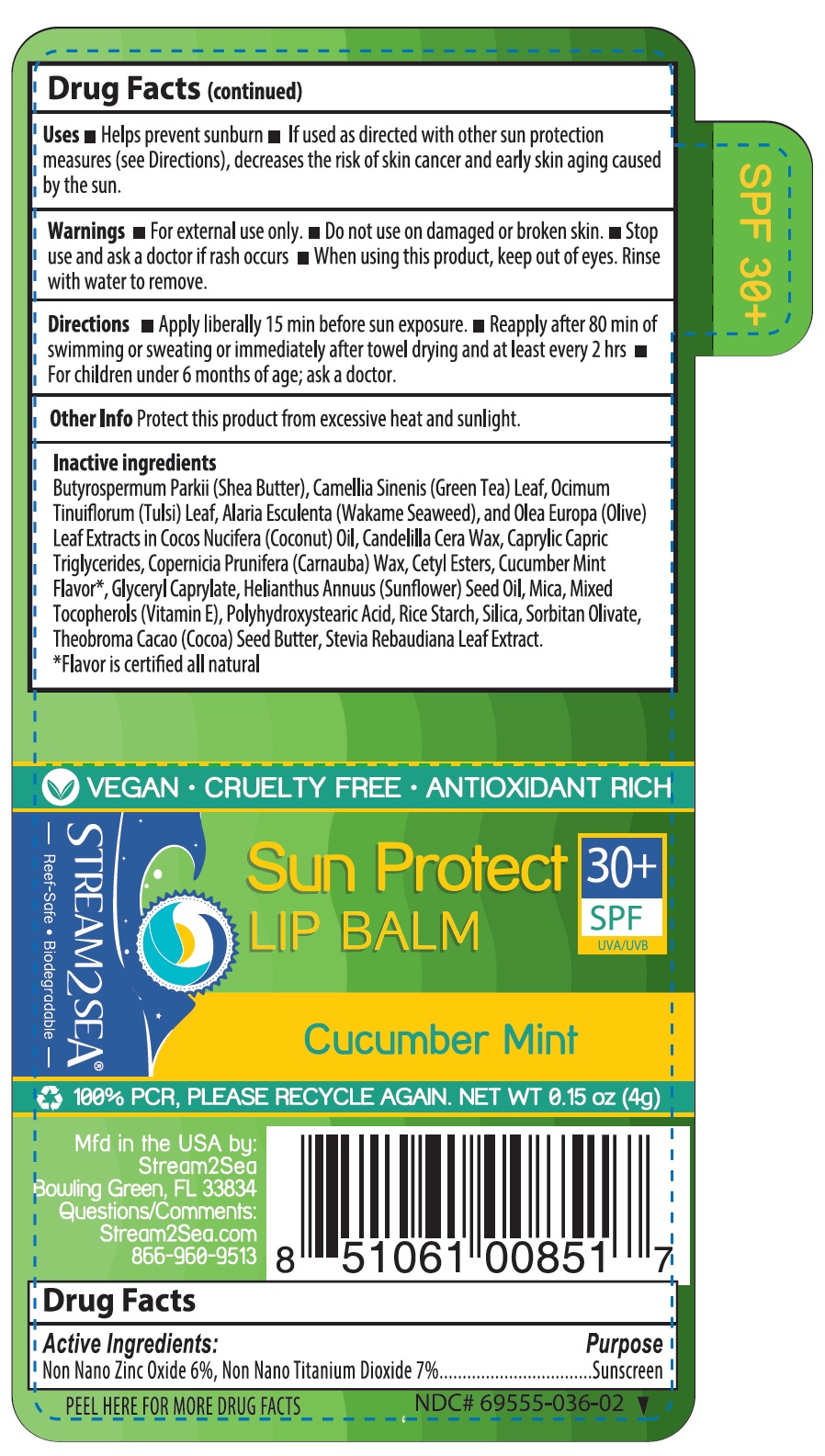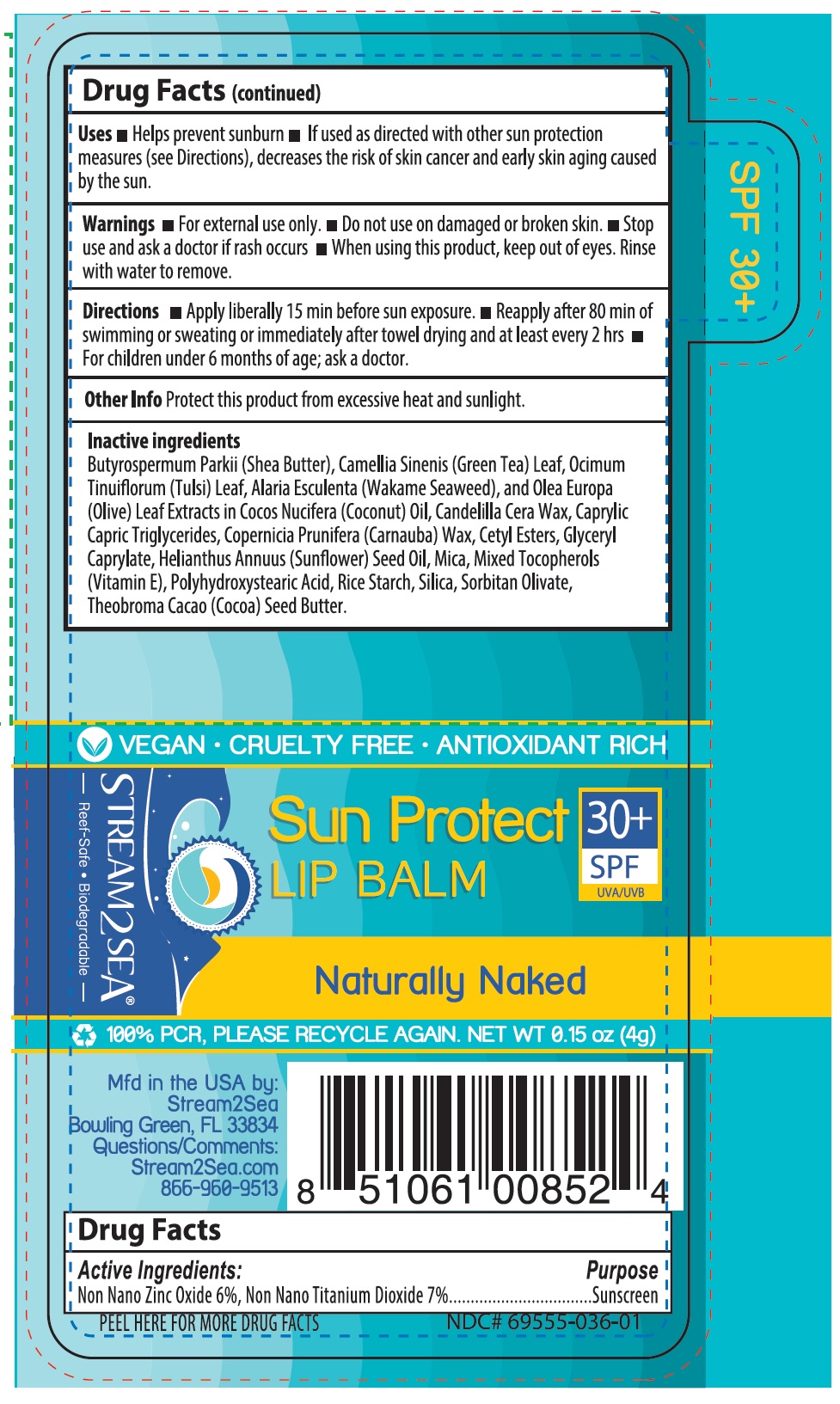 DRUG LABEL: SUN PROTECT LIP BALM SPF 30
NDC: 69555-036 | Form: CREAM
Manufacturer: Stream2Sea, LLC
Category: otc | Type: HUMAN OTC DRUG LABEL
Date: 20250112

ACTIVE INGREDIENTS: TITANIUM DIOXIDE 280 mg/4 g; ZINC OXIDE 240 mg/4 g
INACTIVE INGREDIENTS: SHEA BUTTER; GREEN TEA LEAF; STEVIA REBAUDIUNA LEAF; HOLY BASIL LEAF; ALARIA ESCULENTA; OLEA EUROPAEA LEAF; CANDELILLA WAX; MEDIUM-CHAIN TRIGLYCERIDES; CARNAUBA WAX; CETYL ESTERS WAX; GLYCERYL CAPRYLATE; SUNFLOWER OIL; MICA; TOCOPHEROL; POLYHYDROXYSTEARIC ACID (2300 MW); STARCH, RICE; SILICON DIOXIDE; SORBITAN OLIVATE; COCOA BUTTER

Sun Protected Lip Balm SPF 30^+

Drug Facts

Active ingredients

Non Nano Zinc Oxide 6%, Non Nano Titanium Dioxide 7%

Purpose
Sunscreen

Uses

- Helps prevent sunburn.
- If used as directed with other sun protection measures (see directions), decreases the risk of skin cancer and early skin aging caused by the sun.

Warnings

- For external use only.
- Do not use on damaged or broken skin.
- Stop use and ask a doctor if rash occurs.
- When using this product, keep out of eyes. Rinse with water to remove.
- Keep out of reach of children, If swallowed, get medical help or contact a poison control centre right away.

Directions

- Apply liberally 15 minutes before sun exposure.
- Reapply after 80 minutes of swimming or sweating or immediately after towel drying and at least every 2 hours.
- For children under 6 months of age; ask a doctor.

Other information

- This is a personal care item, and should be used by one individual only.
- Protect this product from excessive heat and direct sun.
- Do not use if safety seal is broken prior to purchase.

Inactive ingredients

Sun Protected Lip Balm SPF 30^+ - Naturally Naked

Butyrospermum Parkii (Shea Butter), Camellis Sinensis (Green Tea) Leaf, Ocimum Tinuiflorum (Tulsi) Leaf, Alaria Esculenta (Wakame Seaweed), and Olea Europa (Olive) Leaf Extracts in Cocos Nucifera (Coconut) Oil, Candelilla Cera Wax, Caprylic Capric Triglycerides, Copernicia Prunifers (Carnuba) Wax, Cetyl Esters, Glyceryl Caprylate, Helianthus Annuus (Sunflower) Seed Oil, Mica, Mixed Tocopherols (Vitamin E), Polyhydroxystearic Acid, Rice Starch, Silica, Sorbitan Olivate, Theobroma Cacao(Cocoa) Seed Butter.

Sun Protected Lip Balm SPF 30^+ - Cherry Vanilla

Butyrospermum Parkii (Shea Butter), Camellis Sinensis (Green Tea)Leaf, Ocimum Tinuiflorum (Tulsi) Leaf, Alaria Esculenta (Wakame Seaweed), and Olea Europa(Olive) Leaf Extracts in Cocos Nucifera (Coconut) Oil, Candelilla Cera Wax, Caprylic Capric Triglycerides, Copernicia Prunifera (Carnauba) Wax, Cetyl esters, Cherry Vanilla Flavor* Glyceryl Caprylate, Helianthus Annuus (Sunflower) Seed Oil, Mica, Mixed Tocopherols (Vitamin E), Polyhydroxystearic Acid, Rice Starch, Silica, Sorbitan Olivate, Theobroma Cacao(Cocoa) Seed Butter, Stevia Rebaudiana Leaf Extract.
*Flavor is certified all natural.

Sun Protected Lip Balm SPF 30^+ - Cucumber Mint

Butyrospermum Parkii (Shea Butter), Camellis Sinensis (Green Tea)Leaf, Ocimum Tinuiflorum (Tulsi) Leaf, Alaria Esculenta (Wakame Seaweed), and Olea Europa (Olive) Leaf Extracts in Cocos Nucifera (Coconut) Oil , Candelilla Cera wax, Caprylic Capric Triglycerides, Copernicia Prunifera (Carnauba) Wax, Cetyl Esters, Cucumber Mint Flavor* Glyceryl Caprylate, Helianthus Annuus(Sunflower) Seed Oil, Mica, Mixed Tocopherols (Vitamin E), Polyhydroxystearic Acid, Rice starch, Silica, Sorbitan Olivate, Theobroma Cacao(Cocoa) Seed Butter, Stevia Rebaudiana Leaf Extract.
*Flavor is certified all natural.

PACKAGE LABEL.PRINCIPAL DISPLAY PANEL

SUN PROTECT LIP BALM NATURALLY NAKED SPF 30^+ 0.15 OZ - Label - NDC - 69555-036-01

SUN PROTECT LIP BALM CUCUMBER MINT SPF 30^+ 0.15 OZ - Label - NDC - 69555-036-02

SUN PROTECT LIP BALM CHERRY VANILLA SPF 30^+ 0.15 OZ - Label - NDC - 69555-036-03